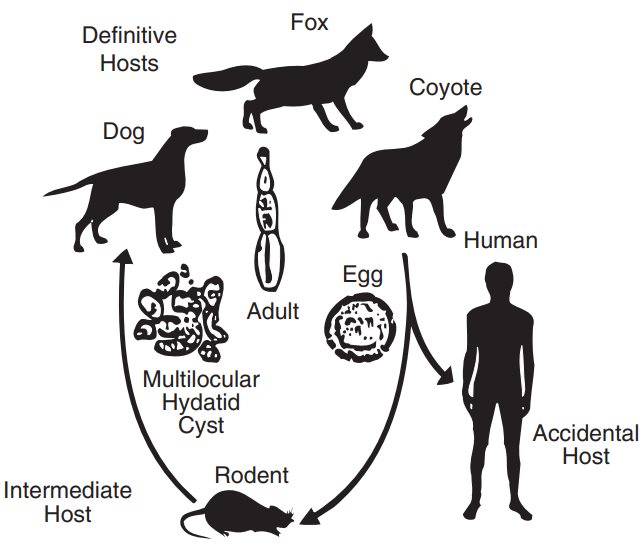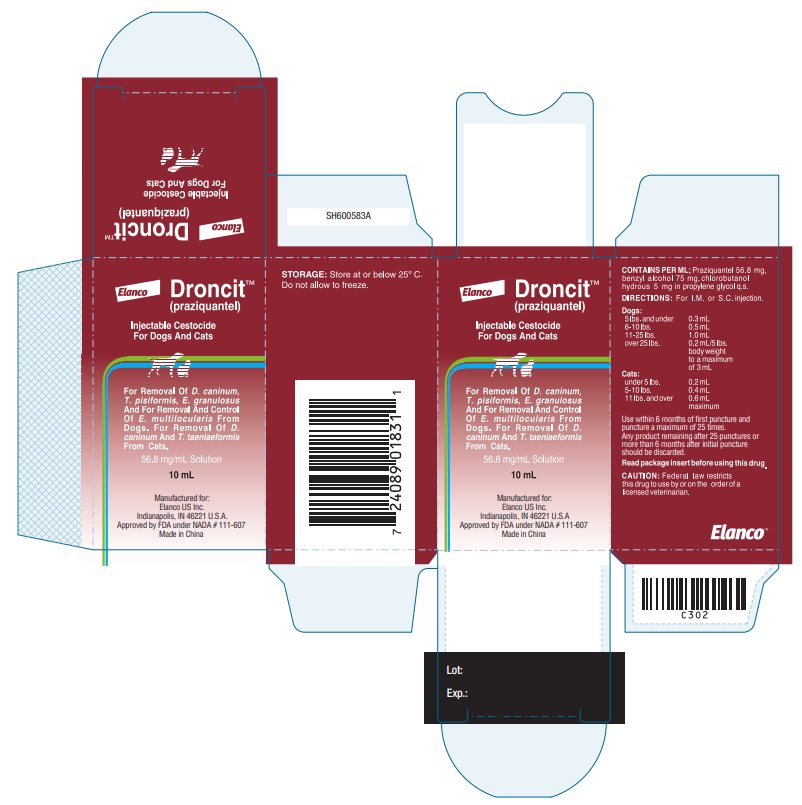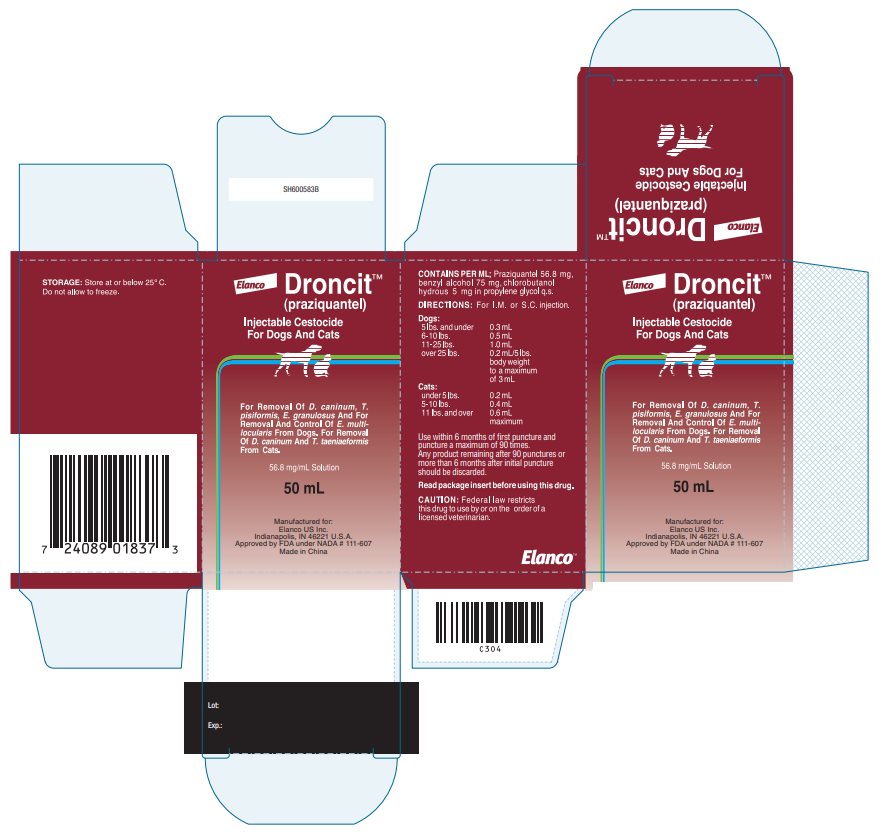 DRUG LABEL: Droncit
NDC: 58198-0031 | Form: INJECTION, SOLUTION
Manufacturer: Elanco US Inc.
Category: animal | Type: PRESCRIPTION ANIMAL DRUG LABEL
Date: 20260223

ACTIVE INGREDIENTS: PRAZIQUANTEL 56.8 mg/1 mL

Elanco
DroncitTM
(praziquantel)
Injectable Cestocide
For Dogs And Cats

56.8 mg/mL Solution

DESCRIPTION:

Droncit Injectable Cestocide is a clear solution containing 56.8 milligrams of praziquantel per mL which has been formulated for subcutaneous or intramuscular use in dogs and cats for removal of cestodes (tapeworms).

INDICATIONS:

Droncit (praziquantel) Injectable Cestocide is indicated for the removal of the following canine and/or feline cestodes. Dogs: Dipylidium caninum, Taenia pisiformis, Echinococcus granulosus and for the removal and control of Echinococcus multilocularis. Cats: Taenia taeniaeformis and Dipylidium caninum.

ACTION:

Droncit (praziquantel) is absorbed, metabolized in the liver and excreted via the bile into the digestive tract where its cestocidal activity is exerted.^1 Following exposure to praziquantel, the tapeworm loses its ability to resist digestion by the mammalian host. Because of this, whole tapeworms, including the scolex, are very rarely passed after administration of praziquantel. It is common to see only disintegrated and partially digested pieces of tapeworms in the stool. The majority of tapeworms killed are digested and are not found in the feces.

USE DIRECTIONS:

Droncit (praziquantel) Injectable Cestocide may be administered by either the subcutaneous or intramuscular route to dogs and cats. The recommended dosage of praziquantel varies according to body weight. Smaller animals require a relatively larger dosage. The optimum dosage for each individual animal will be achieved by utilizing the following dosage schedule.

DOGS AND PUPPIES†
Dogs:
5 lbs. and under | 0.3 mL
6-10 lbs. | 0.5 mL
11-25 lbs. | 1.0 mL
over 25 lbs. | 0.2 mL /5 lbs. body weight to a maximum of 3 mL
† Not intended for use in puppies less than four (4) weeks of age.

CATS AND KITTENS††
Cats:
Under 5 lbs. | 0.2 mL
5-10 lbs. | 0.4 mL
11 lbs. and over | 0.6 mL maximum
†† Not intended for use in kittens less than six (6) weeks of age.

10 mL: Use within 6 months of first puncture and puncture a maximum of 25 times. Any product remaining after 25 punctures or more than 6 months after initial puncture should be discarded.

50 mL: Use within 6 months of first puncture and puncture a maximum of 90 times. Any product remaining after 90 punctures or more than 6 months after initial puncture should be discarded.

FASTING:

The recommended dosage of praziquantel is not affected by the presence or absence of food in the gastrointestinal tract, therefore, FASTING IS NEITHER NECESSARY NOR RECOMMENDED.

ADMINISTRATION:

Droncit (praziquantel) Injectable Cestocide may be administered by either the subcutaneous or intramuscular route to dogs and cats. The intramuscular route may be preferred in dogs due to a brief period of pain that occasionally follows subcutaneous administration.

Anaphylactoid reactions were not observed in clinical trials. However, as with any drug an anaphylactoid reaction can occur with this product and should be treated symptomatically if it occurs.

RETREATMENT:

For those animals living where reinfections are likely to occur, clients should be instructed in the steps to optimize prevention, otherwise, retreatment may be necessary. This is true in cases of Dipylidium caninum where reinfection is almost certain to occur if fleas are not removed from the animal and its environment. In addition, for control of Echinococcus multilocularis, a program of regular treatment every 21 to 26 days may be indicated (see E. multilocularis section below).

ECHINOCOCCUS MULTILOCULARIS:

Echinococcus multilocularis is a tapeworm species ordinarily considered to be found in wild canids, including foxes, coyotes and wolves. The parasite has also been identified in domestic dogs and cats and potentially is a serious public health concern by involving humans as accidental intermediate hosts.

The life cycle of the parasite is based on a predator-prey relationship, as depicted above.

The adult tapeworm is small (1-4mm) and resides in the intestinal tract of the definitive host (wild or domestic canids). Eggs from the adult tapeworm are shed in the feces of the infected canid. Rodents such as mice and voles serve as the intermediate host for E. multilocularis. Eggs ingested by rodents develop in the liver, lungs and other organs to form multilocular cysts. The life cycle is completed after a canid consumes a rodent infected with cysts. After ingestion of the infected rodent, larvae within the cyst develop to adult tapeworms in the intestinal tract of the canid. Eggs may begin to be passed in the feces of the canid approximately 28 days later.

This parasite poses a serious public health problem because of the possibility for human involvement in the life cycle. If eggs shed by an infected canid are accidentally ingested, a highly pathogenic condition (Alveolar Hydatid Disease) results from development of the cyst stage in humans.

The original geographic distribution of E. multilocularis was primarily confined to northern areas of North America. Current evidence indicates migration of the parasite well into the continental United States.^2,3

Domestic dogs living in E. multilocularis endemic areas that roam freely with the opportunity to catch wild rodents are at risk for infection. Pet owners should be advised on how to minimize this risk. Proper restraint of roaming dogs should be encouraged, along with regular treatment with Droncit Injectable solution, following the dosing schedule aforementioned and precautions indicated below.

Additional information on the life cycle and epidemiology of this parasite is available in veterinary parasitology texts.^4,5

Diagnosis:

Diagnosis of E. multilocularis in canids is difficult. The adult tapeworm produces no clinical signs of infection. Tapeworm segments (proglottids) are usually not observed in the feces. E. multilocularis eggs, observed using microscopic fecal examination procedures, are similar in appearance to the common taeniid species of canids such as Taenia pisiformis.

Assistance in the diagnosis of E. multilocularis may be available from a state veterinary diagnostic laboratory. Additional information regarding areas where E. multilocularis is suspected or has been confirmed may be obtained from area veterinary schools or the Centers for Disease Control in Atlanta, GA.

Treatment:

Dogs infected with E. multilocularis should be treated to prevent exposure of humans to infective eggs and to reduce perpetuation of the parasite’s life cycle.

The dosage of Droncit Injectable solution for removal of E. multilocularis is the same as that indicated for the removal of the other tapeworm species listed on the label. Laboratory efficacy studies have demonstrated the recommended dosage is 100% efficacious for removal of this tapeworm.

Under condition of continual exposure to wild rodents, retreatment of the dog at 21-26 day intervals is recommended to prevent the shedding of infectious eggs.

Precautions:

Strict hygienic precautions should be taken when handling dogs or feces suspected of harboring E. multilocularis. Infected dogs treated for the first time with Droncit Injectable solution and dogs treated at intervals greater than 28 days may shed eggs in the feces after treatment. The animal should be held in the clinic during this interval and all feces should be incinerated or autoclaved. If these procedures are not possible, the eggs can be destroyed by soaking the feces in a sodium hypochlorite (bleach) solution of 3.75% or greater.^6 All areas where the animal was maintained or in contact with should be thoroughly cleaned with sodium hypochlorite and allowed to dry completely before reuse.

OVERDOSAGE:

The safety index has been derived from controlled safety evaluations, clinical trials and prior approved use in foreign countries. Dosages of 5 times the labeled rate at 14 day intervals to dogs as young as 4 weeks did not produce signs of clinical toxicity following either intramuscular or subcutaneous injections. No significant clinical chemistry, hematological, cholinesterase or histopathological changes occurred. Dosages of 5 times the labeled rate at 14 day intervals to kittens as young as 5 1/2 weeks did not produce signs of clinical toxicity following either intramuscular or subcutaneous injections. Symptoms of overdosage (33.8 to 40 times the labeled dosage rate) in adult dogs included vomition, excessive salivation and depression, but no deaths. Symptoms of overdosage (10 to 20 times the labeled dosage rate) in adult cats included vomition, depression, muscle tremors and incoordination. Deaths occurred in 5 of 8 cats treated subcutaneously and in all 8 injected intramuscularly at doses greater than 20 times the label rate.

CONTRAINDICATIONS:

There are no known contraindications to the use of praziquantel.

PREGNANCY:

Droncit (praziquantel) has been tested in breeding and pregnant dogs and cats. No adverse effects were noted.

ADVERSE REACTIONS:

Mild side effects were observed in 18 of 189 dogs (9.5%) and 8 of 85 cats (9.4%) administered Droncit Injectable in field trials. For dogs the majority of these were described as brief pain responses following injections to larger dogs (weighing over 50 lbs.). Two dogs exhibited a brief period of mild vomiting and/or drowsy or staggering gait. The eight cats exhibited either diarrhea, weakness, vomition, salivation, sleepiness, burning on injection and/or a temporary lack of appetite. Local irritation or swelling at the site of subcutaneous injections have been reported for cats.

CONTACT INFORMATION:

For product questions, or to report adverse reactions, or for a copy of the Safety Data Sheet (SDS), call Elanco Product and Veterinary Support at 888-545-5973.

For additional information about reporting adverse drug experiences for animal drugs, contact FDA at 1-888-FDA-VETS or http://www.fda.gov/reportanimalae.

CAUTION:

Federal law restricts this drug to use by or on the order of a licensed veterinarian.

STORAGE CONDITIONS:

Store at or below 25º C. Do not allow to freeze.

HOW SUPPLIED:

Code: | 10 mL vial
 | 50 mL vial

REFERENCES:

1. Andrews P. Pharmacokinetic Studies with DRONCIT in Animals Using a Biological Assay. Veterinary Medical Review, 2/76, pg. 154-165.
2. Hildreth MB, Johnson MD and Kazacos KR. 1991. A Zoonosis of Increasing Concern in the United States. Compendium for Cont Ed, 13(5) 727-740.
3. Lieby PD, Carney WP and Woods CE. 1970. Studies on Sylvatic Echinococcosis. III. Host Occurrence and Geographic Distribution of Echinococcus multilocularis in the North Central United States. J Parasit 56 (6) 1141-1150.
4. Georgi JR and Georgi ME. 1990. Parasitology for Veterinarians. W.B. Saunders Co. 118-138.
5. Soulsby EJL. 1982. Helminths, Arthropods and Protozoa of Domesticated Animals. 7th Edition. Lea & Febigir. 118-138.
6. Craig PS and McPharson CNL. 1988. Sodium Hypochlorite as an Ovicide for Echinococcus. Ann Trop Med and Parasit 82(2) 211-213.

Manufactured for:
Elanco US Inc.
Indianapolis, IN 46221 U.S.A.

Droncit, Elanco and the diagonal bar logo are trademarks of Elanco or its affiliates.
Revised: November 2025
© 2025 Elanco or its affiliates.
Approved by FDA under NADA # 111-607
PA600583X

Elanco™

Principal Display Panel

Elanco

DroncitTM

(praziquantel)

Injectable Cestocide
For Dogs And Cats

For Removal Of D. caninum,
T. pisiformis, E. granulosus
And For Removal And Control
Of E. multilocularis From
Dogs. For Removal Of D.
caninum And T. taeniaeformis
From Cats.

56.8 mg/mL Solution

10 mL

Manufactured for:
Elanco US Inc.
Indianapolis, IN 46221 U.S.A
Approved by FDA under NADA # 111-607
Made in China

Elanco

DroncitTM

(praziquantel)

Injectable Cestocide
For Dogs And Cats

For Removal Of D. caninum, T.
pisiformis, E. granulosus And For
Removal And Control Of E. multi-
locularis From Dogs. For Removal
Of D. caninum And T. taeniaeformis
From Cats.

56.8 mg/mL Solution

50 mL

Manufactured for:
Elanco US Inc.
Indianapolis, IN 46221 U.S.A.
Approved by FDA under NADA # 111-607
Made in China